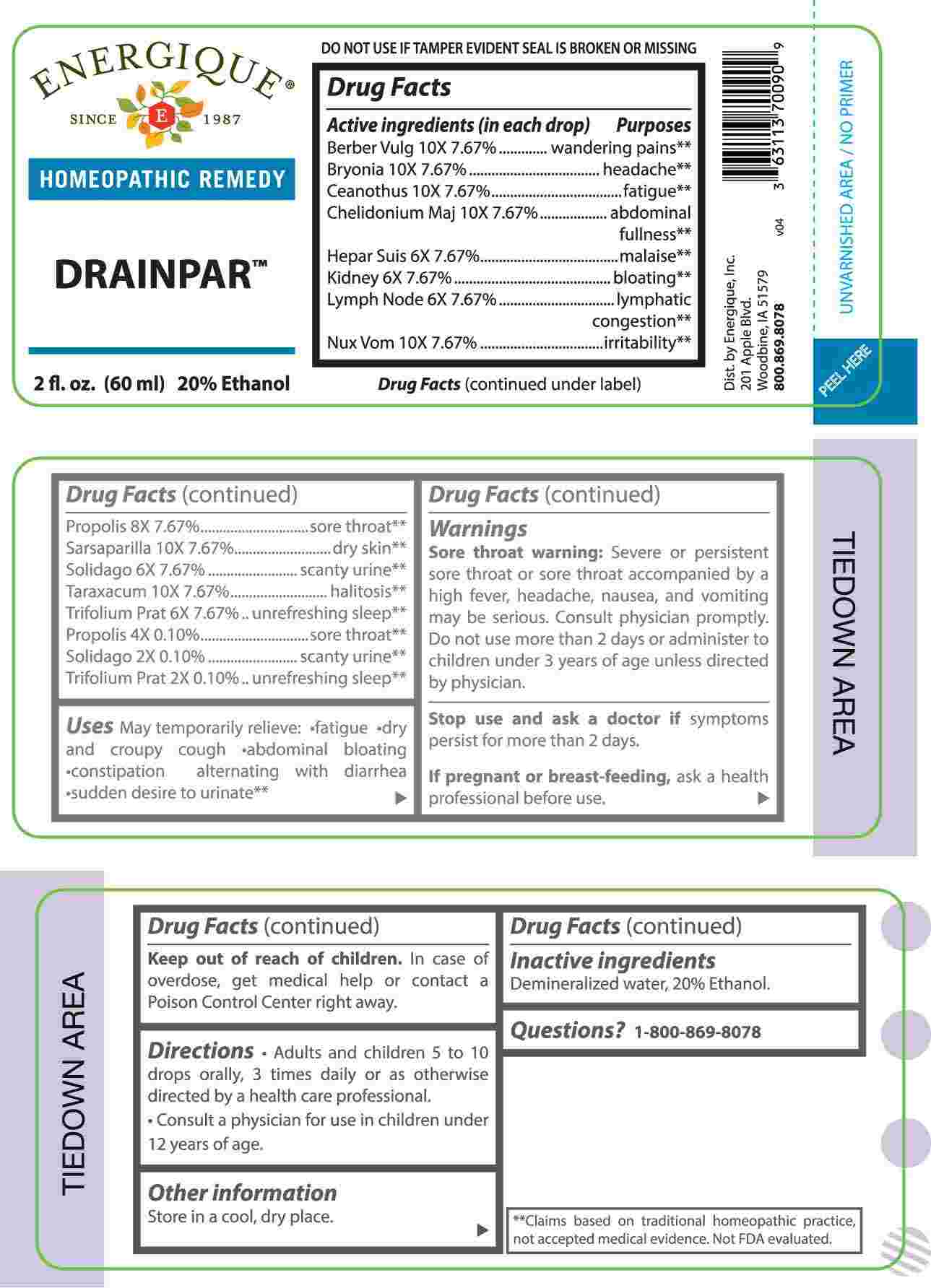 DRUG LABEL: Drainpar
NDC: 44911-0731 | Form: LIQUID
Manufacturer: Energique, Inc.
Category: homeopathic | Type: HUMAN OTC DRUG LABEL
Date: 20250318

ACTIVE INGREDIENTS: SOLIDAGO VIRGAUREA FLOWERING TOP 2 [hp_X]/1 mL; TRIFOLIUM PRATENSE FLOWER 2 [hp_X]/1 mL; PROPOLIS WAX 4 [hp_X]/1 mL; PORK LIVER 6 [hp_X]/1 mL; PORK KIDNEY 6 [hp_X]/1 mL; SUS SCROFA LYMPH 6 [hp_X]/1 mL; BERBERIS VULGARIS ROOT BARK 10 [hp_X]/1 mL; BRYONIA ALBA ROOT 10 [hp_X]/1 mL; CEANOTHUS AMERICANUS LEAF 10 [hp_X]/1 mL; CHELIDONIUM MAJUS WHOLE 10 [hp_X]/1 mL; STRYCHNOS NUX-VOMICA SEED 10 [hp_X]/1 mL; SMILAX ORNATA ROOT 10 [hp_X]/1 mL; TARAXACUM OFFICINALE 10 [hp_X]/1 mL
INACTIVE INGREDIENTS: WATER; ALCOHOL

DRUG FACTS:

ACTIVE INGREDIENTS:

(in each drop) Berberis Vulgaris 10X 7.67%, Bryonia 10X 7.67%, Ceanothus Americanus 10X 7.67%, Chelidonium Majus 10X 7.67%, Hepar Suis 6X 7.67%, Kidney 6X 7.67%, Lymph Node 6X 7.67%, Nux Vomica 10X 7.67%, Propolis 8X 7.67%, Sarsaparilla 10X 7.67%, Solidago Virgaurea 6X 7.67%, Taraxacum Officinale 10X 7.67%, Trifolium Pratense 6X 7.67%, Propolis 4X 0.10%, Solidago Virgaurea 2X 0.10%, Trifolium Pratense 2X 0.10%

PURPOSE:

Berberis Vulgaris - wandering pain,** Bryonia - headache,** Ceanothus Americanus - fatigue,** Chelidonium Majus – abdominal fullness,** Hepar Suis - malaise,** Kidney - bloating,** Lymph Node – lymphatic congestion ,** Nux Vomica - irritability,** Propolis – sore throat,** Sarsaparilla – dry skin,** Solidago Virgaurea – scanty urine,** Taraxacum Officinale - halitosis,** Trifolium Pratense – unrefreshing sleep,**

USES:

May temporarily relieve: •fatigue •dry and croupy cough •abdominal bloating •constipation alternating with diarrhea •sudden desire to urinate**

**Claims based on traditional homeopathic practice, not accepted medical evidence. Not FDA evaluated.

WARNINGS:

Sore throat warning: Severe or persistent sore throat or sore throat accompanied by a high fever, headache, nausea, and vomiting may be serious. Consult physician promptly. Do not use more than 2 days or administer to children under 3 years of age unless directed by physician.

Stop use and ask a doctor if symptoms persist for more than 2 days.

If pregnant or breast-feeding, ask a health professional before use.

Keep out of reach of children. In case of overdose, get medical help or contact a Poison Control Center right away.

DO NOT USE IF TAMPER EVIDENT SEAL IS BROKEN OR MISSING

Store in a cool, dry place.

KEEP OUT OF REACH OF CHILDREN:

In case of overdose, get medical help or contact a Poison Control Center right away.

DIRECTIONS:

• Adults and children 5 to 10 drops orally, 3 times daily or as otherwise directed by a health care professional.

• Consult a physician for use in children under 12 years of age.

INACTIVE INGREDIENTS:

Demineralized water, 20% Ethanol.

QUESTIONS:

Dist. by Energique, Inc.

201 Apple Blvd.

Woodbine, IA 51579

800-869-8078

PACKAGE LABEL DISPLAY:

ENERGIQUE

SINCE 1987

HOMEOPATHIC REMEDY

DRAINPAR

2 fl. oz. (60 ml)